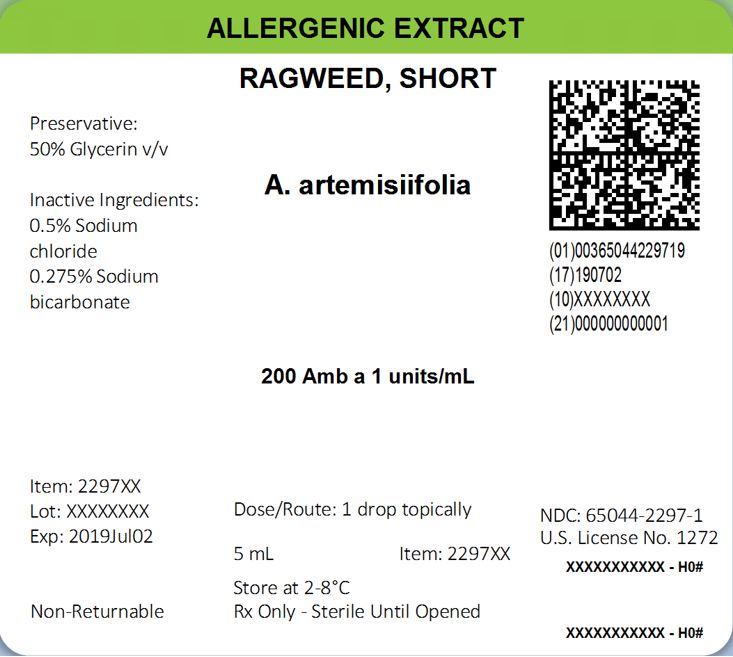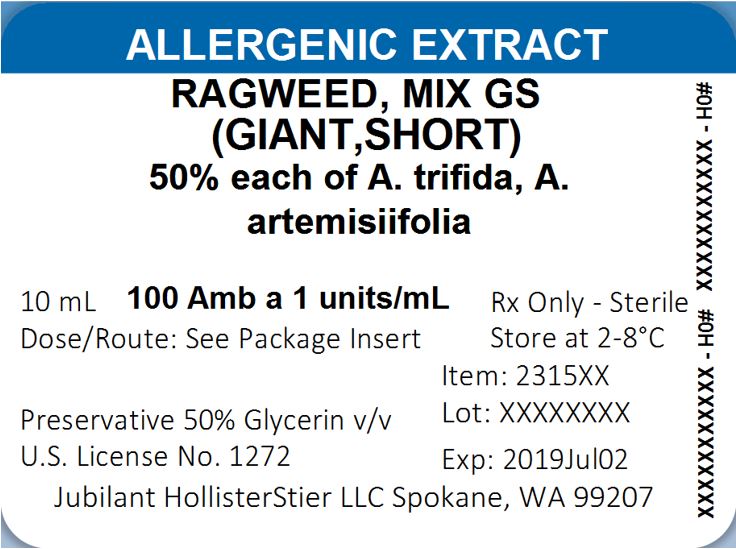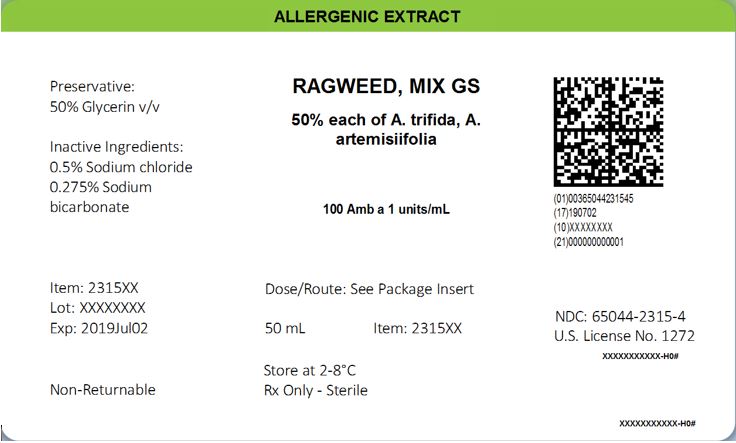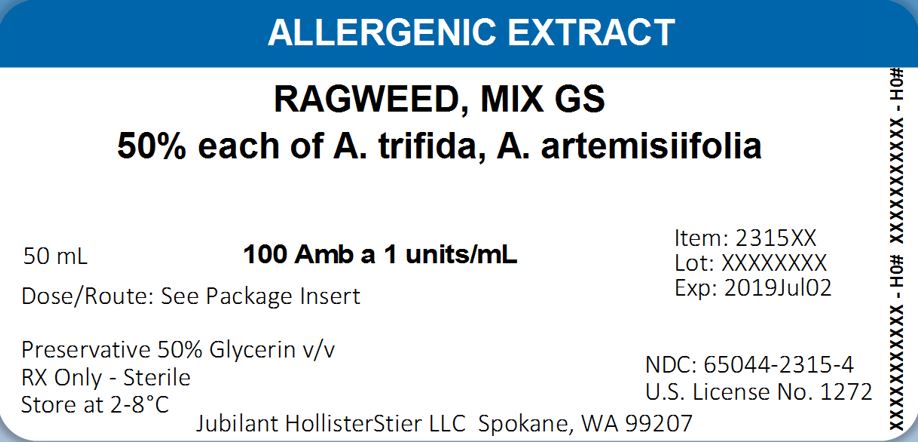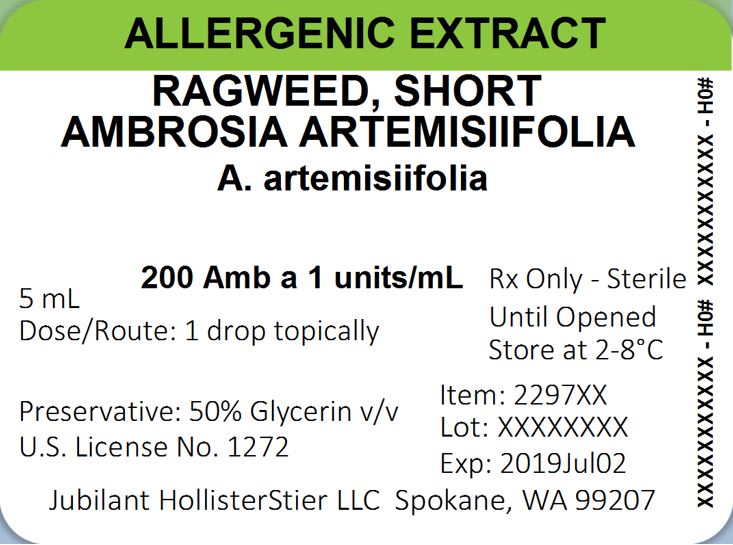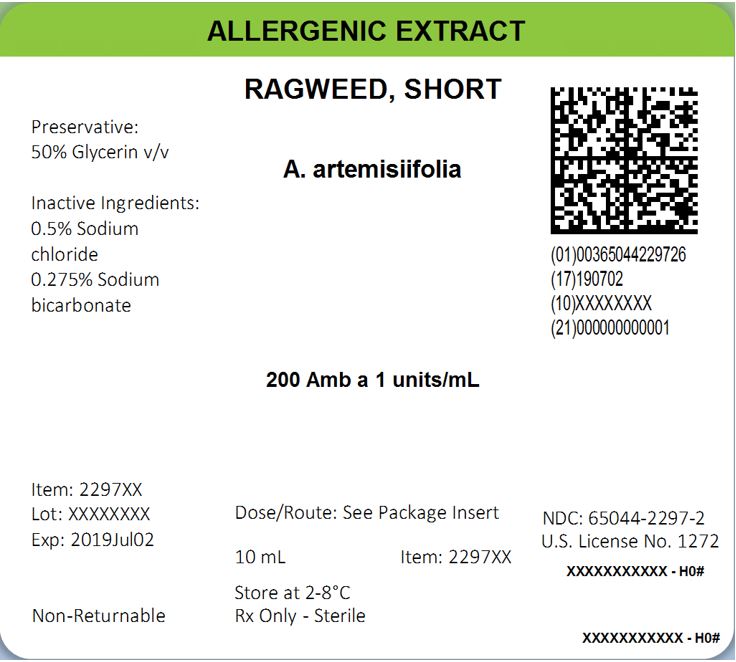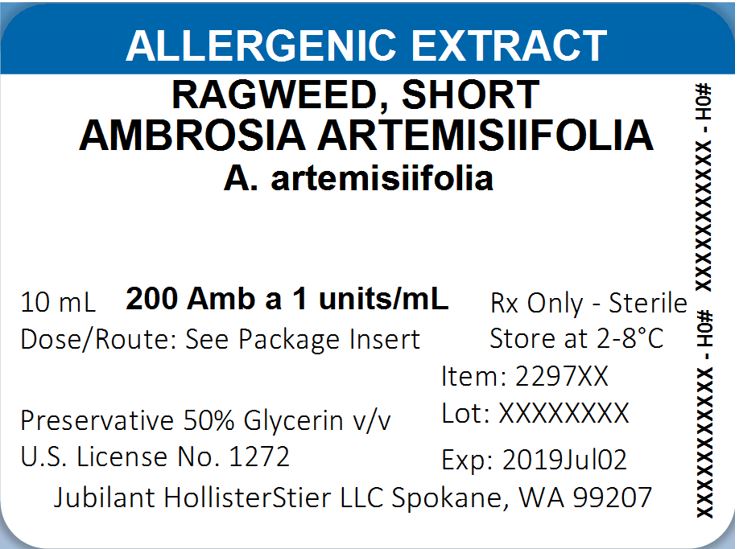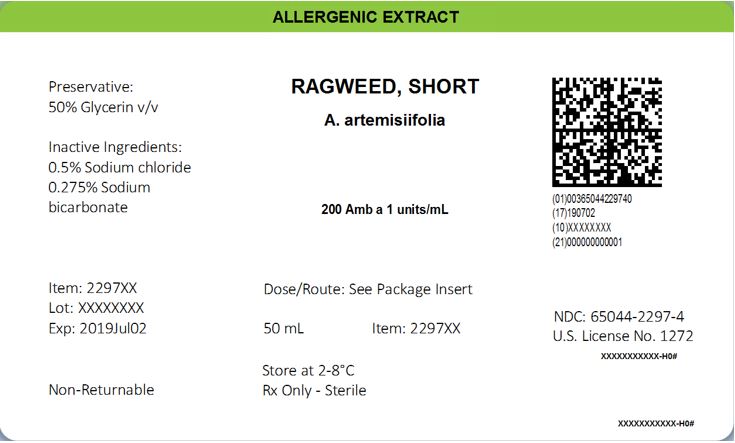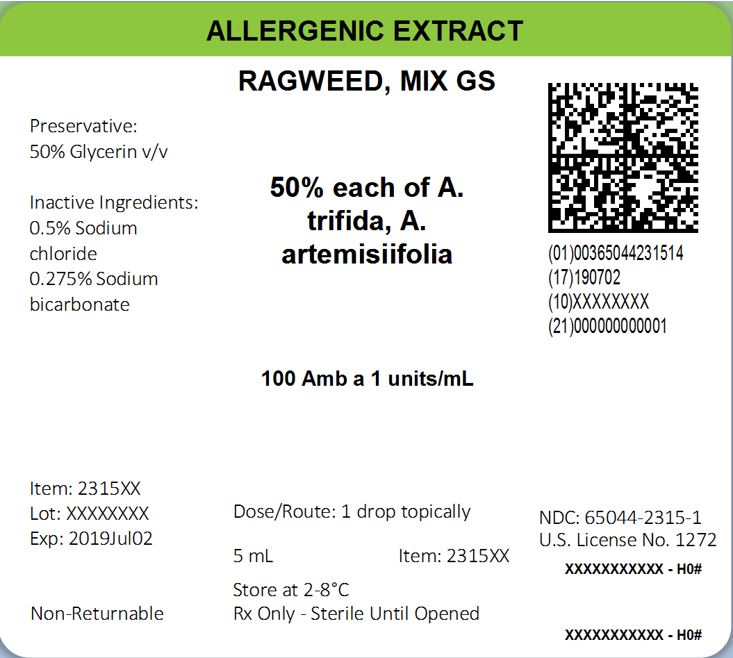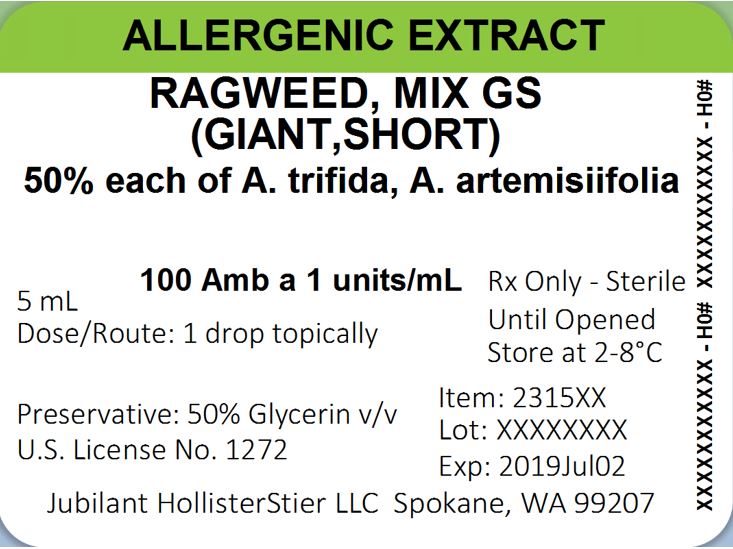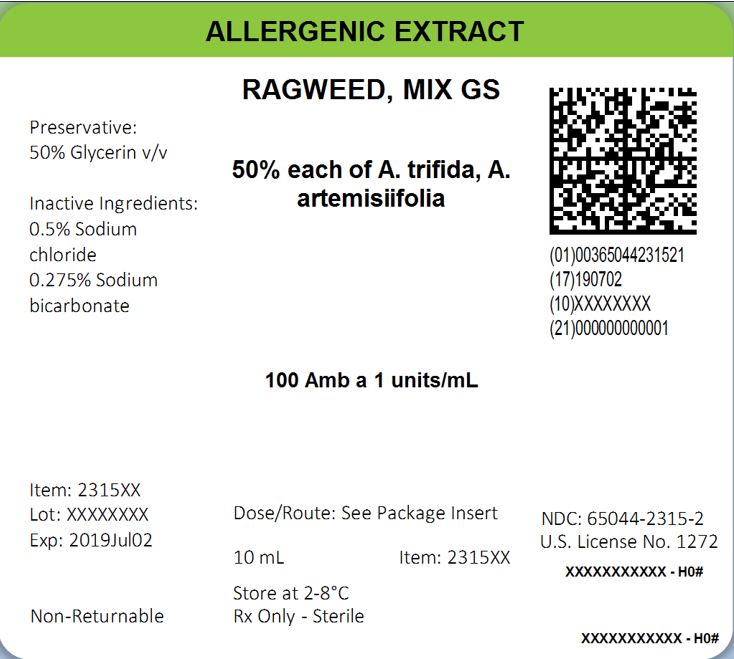 DRUG LABEL: Pollens - Weeds and Garden Plants, Short Ragweed, Ambrosia artemisiifolia
NDC: 65044-2297 | Form: INJECTION, SOLUTION
Manufacturer: Jubilant HollisterStier LLC
Category: other | Type: STANDARDIZED ALLERGENIC
Date: 20251119

ACTIVE INGREDIENTS: AMBROSIA ARTEMISIIFOLIA POLLEN 0.05 g/1 mL
INACTIVE INGREDIENTS: GLYCERIN; SODIUM CHLORIDE; SODIUM BICARBONATE

HIGHLIGHTS OF PRESCRIBING INFORMATION

These highlights do not include all the information needed to use SHORT RAGWEED POLLEN ALLERGENIC EXTRACT AND SHORT AND GIANT RAGWEED POLLEN MIX ALLERGENIC EXTRACT safely and effectively. See full prescribing information for SHORT RAGWEED POLLEN ALLERGENIC EXTRACT AND SHORT AND GIANT RAGWEED POLLEN MIX ALLERGENIC EXTRACT.
SHORT RAGWEED POLLEN ALLERGENIC EXTRACT AND SHORT AND GIANT RAGWEED POLLEN MIX ALLERGENIC EXTRACT
Solution for percutaneous, intradermal, or subcutaneous administration Initial U.S. Approval: 1925

WARNING: ANAPHYLAXIS

See full prescribing information for complete boxed warning.

- Short Ragweed Pollen Allergenic Extract and Short and Giant Ragweed Pollen Mix Allergenic Extract can cause anaphylaxis, including anaphylactic shock and death (5.1)
- Do not administer to individuals with:
  - severe, unstable or uncontrolled asthma;
  - history of severe systemic reaction to the allergen extract when administered for diagnosis or treatment;
  - medical condition that reduces the ability to survive anaphylaxis. (4)
- Observe individuals for at least 30 minutes following administration. Emergency measures and personnel trained in their use must be available in the event of a life-threatening reaction. (5.1)
- Individuals with extreme sensitivity to these products, on an accelerated immunotherapy build-up, switching to another lot, receiving high doses of these products, or exposed to similar allergens may be at increased risk of anaphylaxis. (5.1)
- These products may not be suitable for individuals who may be unresponsive to epinephrine or inhaled bronchodilators, such as those taking beta-blockers. (5.1)

1 INDICATIONS AND USAGE

Short Ragweed Pollen Allergenic Extract and Short and Giant Ragweed Pollen Mix Allergenic Extract are indicated for:

- Skin test diagnosis of patients with a clinical history of allergy to ragweed pollen (Short Ragweed or Short and Giant Ragweed pollen). (1)
- Immunotherapy for the reduction of ragweed pollen-induced allergic symptoms confirmed by positive skin test or by in vitro testing for pollen-specific IgE antibodies for Short and/or Giant Ragweed Pollen. (1)

2 DOSAGE AND ADMINISTRATION

For percutaneous, intradermal, or subcutaneous use only.

Administration:

- Percutaneous for diagnostic testing.
- Intradermal for diagnostic testing.
- Subcutaneous for immunotherapy.

See full prescribing information for details on dosing and dilution preparation. (2)

3 DOSAGE FORMS AND STRENGTHS

Short Ragweed Pollen Allergenic Extract solution and Short and Giant Ragweed Pollen Mix Allergenic Extract solution: stock concentrate, labeled as Amb a 1 Units/mL, in a glycerin-preserved extracting fluid, supplied in 5 mL dropper vial, and 10 and 50 mL multidose vials. (3, 16)

Refer to the vial label for the product concentration. (11)

4 CONTRAINDICATIONS

- Severe, unstable or uncontrolled asthma. (4)
- History of any severe systemic reaction to the allergen extract when administered for diagnosis or treatment. (4)
- Medical condition that reduces the ability to survive anaphylaxis. (4)

5 WARNINGS AND PRECAUTIONS

The risk of anaphylaxis may be increased in the following situations:

- Extreme sensitivity to Short Ragweed Pollen and Short and Giant Ragweed Pollen Mix allergenic extracts.
- Concomitant environmental exposure to similar allergens.
- Receipt of high concentrations and volumes of Short Ragweed Pollen and Short and Giant Ragweed Pollen Mix allergenic extracts.
- Receipt of an accelerated build-up schedule (e.g., "rush" immunotherapy).
- Changing to another lot of allergen. (5)

6 ADVERSE REACTIONS

Common adverse reactions reported for Short Ragweed Pollen Allergenic Extract and Short and Giant Ragweed Pollen Mix Allergenic Extract are:

- Local adverse reactions, occurring in 26 to 82% of all patients who receive subcutaneous immunotherapy (e.g., erythema, swelling, pruritus, tenderness and pain at the injection site). (6)
- Systemic adverse reactions occurring in ≤ 7% of patients who receive subcutaneous immunotherapy (e.g., generalized skin erythema, urticaria, pruritus, angioedema, rhinitis, wheezing, laryngeal edema,hypotension, and shock).Systemic reactions may be fatal. (6)

To report SUSPECTED ADVERSE REACTIONS, contact Jubilant HollisterStier at 1-800-495-7437 or Adverse.Reactions@jubl.com; or the FDA at 1-800-FDA-1088 or www.fda.gov/medwatch

7 DRUG INTERACTIONS

Certain medications may decrease skin test wheal and erythema responses, including antihistamines, topical corticosteroids, topical anesthetics, and tricyclic antidepressants. (7)

FULL PRESCRIBING INFORMATION

WARNING: ANAPHYLAXIS

- Short Ragweed Pollen or Short and Giant Ragweed Pollen Mix allergenic extracts can cause anaphylaxis, including anaphylactic shock and death. (5.1)
- Do not administer to individuals with:
  - severe, unstable or uncontrolled asthma;
  - history of severe systemic reaction to the allergen extract when administered for diagnosis or treatment;
  - medical condition that reduces the ability to survive anaphylaxis. (4)
- Observe individuals for at least 30 minutes following administration.Emergency measures and personnel trained in their use must be available in the event of a life-threatening reaction. (5.1)
- Individuals with extreme sensitivity to these products, on an accelerated immunotherapy build-up, switching to another lot, receiving high doses of these products, or exposed to similar allergens may be at increased risk of anaphylaxis. (5.1)
- These products may not be suitable for individuals who may be unresponsive to epinephrine or inhaled bronchodilators, such as those taking beta-blockers. (5.1)

1 INDICATIONS AND USAGE

SHORT RAGWEED POLLEN ALLERGENIC EXTRACT and SHORT AND GIANT RAGWEED POLLEN MIX ALLERGENIC EXTRACT are indicated for:

- Skin test diagnosis of patients with a clinical history of allergy to ragweed pollen (Short Ragweed or Short and Giant Ragweed Pollen).
- Immunotherapy for the reduction of ragweed pollen-induced allergic symptoms confirmed by positive skin test or by in vitro testing for pollen-specific IgE antibodies for Short and/or Giant Ragweed pollen.

2 DOSAGE AND ADMINISTRATION

For percutaneous, intradermal, or subcutaneous administration only. Do not inject intravenously.

2.1 Preparation for Administration

Appearance is clear to slightly opalescent. Parenteral drug products should be inspected visually for particulate matter and discoloration prior to administration, whenever solution and container permit. Discard solution if either of these conditions exist.

Short Ragweed Pollen and Short and Giant Ragweed Pollen Mix allergenic extracts diluted with Albumin Saline with Phenol (0.4%) (stabilized diluent) may be more potent than extracts diluted with diluents that do not contain albumin. When switching from non-stabilized to stabilized diluent, consider less concentrated initial dilutions for both intradermal testing and immunotherapy.

Different formulations, preparations, or new lots of Short Ragweed Pollen and Short and Giant Ragweed Pollen Mix allergenic extracts are not interchangeable. Dosing should be adjusted appropriately when formulations, preparations, or lots of Short Ragweed Pollen and Short and Giant Ragweed Pollen Mix allergenic extracts are changed [see Immunotherapy (2.3) and Dosage Forms and Strengths (3)].

Allergenic extracts may be prepared for intradermal (diagnosis) or subcutaneous (immunotherapy) administration by diluting stock concentrates.

- For diluent, use sterile albumin saline with phenol or sterile normal saline with phenol.
- Dilute stock concentrates by a minimum of 100-fold for intradermal testing. Dilutions of 1,000-fold or greater are appropriate starting points for patients with a clinical history of adverse reaction.

To prepare dilutions for intradermal testing and immunotherapy, start with a stock concentrate, and prepare a ten-fold (1:10) dilution by adding 0.5 mL of concentrate to 4.5 mL of sterile aqueous diluent. Prepare subsequent dilutions in a similar manner. (see Table 1)

Table 1: 10-fold Dilution Series

Dilution | Extract | Milliliters of Diluent | Dilution Strength; Amb a 1 Units/mL
Dilution | Extract | Milliliters of Diluent | Short Ragweed Pollen | Short and Giant Ragweed Pollen Mix
0 | Concentrate |  | 200 | 100
1 | 0.5 mL Concentrate | 4.5 | 20 | 10
2 | 0.5 mL Dilution 1 | 4.5 | 2 | 1
3 | 0.5 mL Dilution 2 | 4.5 | 0.2 | 0.1
4 | 0.5 mL Dilution 3 | 4.5 | 0.02 | 0.01
5 | 0.5 mL Dilution 4 | 4.5 | 0.002 | 0.001
6 | 0.5 mL Dilution 5 | 4.5 | 0.0002 | 0.0001
Note: A lower starting dose and/or less concentrated dilutions may be necessary for highly sensitive patients with a clinical history of sensitivity, or for those who display severe symptoms. [see Diagnostic Testing (2.2), Percutaneous Skin Testing (2.2.1) and Intradermal (Intracutaneous) Skin Test (2.2.2)].

2.2 Diagnostic Testing

Testing is performed to identify patients that exhibit an allergic response at the site of administration. False positive reactions may occur. A positive skin test reaction must be interpreted in the context of the individual’s clinical history and known exposure to the allergen.

- Administer percutaneous tests prior to administration of intradermal tests to identify highly sensitive patients.
- Do not use allergen mixes for diagnostic testing because a positive reaction would not permit specific identification of the allergen(s) that elicited the reaction. In addition, a negative reaction would fail to indicate whether an individual component allergen would have elicited a positive reaction at full strength.

2.2.1 Percutaneous Skin Testing

Dose

Unless an individual is suspected to be at greater risk for anaphylaxis, the initial starting dose is 1 drop (approximately 0.05 mL) of undiluted allergenic extract. For individuals suspected to be at greater risk for anaphylaxis (for example, as indicated by a history of allergen-induced anaphylaxis), initiate percutaneous testing with a sequence of serial 10-fold dilutions of undiluted allergenic extract spaced 15-20 minutes apart [see Preparation for Administration (2.1)].

Administration

- Percutaneous Test: Place one drop (approximately 0.05 mL) of allergen on the skin and pierce through drop superficially into the skin, lifting slightly. Use a skin test device, such as a sterile needle, lancet, or bifurcated needle.
- Percutaneous Test using self-loading devices: Refer to the manufacturer’s product instructions.

Concurrently, use a positive histamine skin test control to identify patients whose recent use of drugs with antihistamine activity may result in a false negative skin test. Apply a 50% glycerin solution as a negative control to identify false positive responses to the extracting fluid used in the manufacture of allergenic extracts, or due to dermographism [see Drug Interactions (7)].

Interpreting Results

For interpretation of percutaneous skin tests, refer to the information provided in Allergy Diagnostic Testing: An Updated Practice Parameter.^1 In addition, follow the directions provided with the percutaneous skin test devices. Measure wheal responses for the histamine positive control test at 15 minutes and for allergen tests at 15 to 20 minutes.

- The negative control (50% glycerin solution) response should measure <3-mm wheal and ≤10 mm flare (erythema).
- Response to the positive control should be at least 3 millimeters larger than the response to the negative control.
- If either the response to the histamine positive control or to the negative control do not meet the criteria above for acceptable wheal size, the results for the allergenic extracts tested at the same time should be considered invalid.

Criteria for interpretation of positive and negative results of percutaneous allergen tests (wheal diameter) are specific to the percutaneous device used to administer percutaneous tests (Reference 1, Table 2, Page S16).

2.2.2 Intradermal (Intracutaneous) Skin Test

Always perform percutaneous skin tests prior to intradermal skin tests.^(1, 2)

Dose

Perform intradermal tests with at least 100-fold less concentrated solutions than the stock concentrates used in percutaneous tests [see Preparation and Administration (2.1)].

Use intradermal tests following a negative or equivocal percutaneous test when the patient continues to report a history of symptoms following exposure to Short and/or Giant Ragweed allergen.

Administration

Intradermally inject 0.02 mL of the allergen using a 1 mL intradermal testing syringe with a 26 or 27 gauge, 1/2" or 3/8" needle with intradermal bevel, graduated in 0.01 units. Insert needle at a 30˚ angle, bevel down.

Test concurrently with a positive histamine control at intradermal strength (0.1 mg/mL of histamine base) and an aqueous buffer negative control (Sterile Albumin Saline with Phenol, Sterile Buffered Saline with Phenol).

Interpreting Results

For interpretation of intradermal skin tests, refer to the information provided in Allergy Diagnostic Testing: An Updated Practice Parameter.^1

- Measure wheal responses for the histamine positive control test and allergen tests at 10-15 minutes after injection Response to the positive control should be at least 3 millimeters greater than the response to the negative control.
- The negative control (50% glycerin solution) response should measure <3-mm wheal and ≤10 mm flare (erythema).
- If either the response to the histamine positive control or to the negative control do not meet the criteria above for acceptable wheal size, the results for the allergenic extracts tested at the same time should be considered invalid.

2.3 Immunotherapy

For subcutaneous administration only.

Administration of Immunotherapy

Administer immunotherapy by subcutaneous injection in the lateral aspect of the arm or thigh. Avoid injection directly into any blood vessels. Administer injections with a sterile 1 mL allergy treatment syringe with a 26 or 27 gauge, 1/2", beveled needle, graduated in 0.01 units.

The optimal interval between doses of allergenic extract varies among individuals. Injections are usually given one or two times per week until the maintenance dose is reached, at which time the injection interval is increased to 2, 3, and finally 4 weeks.

Most adverse reactions occur within 30 minutes after injection. Therefore, observe patients for at least 30 minutes. For high risk patients, 30 minutes of observation may not be sufficient.^2

Dosing of Short Ragweed Pollen and Short and Giant Ragweed Pollen Mix allergenic extracts for allergen immunotherapy is highly individualized. Adjust dose according to the degree of sensitivity of the patient, tolerance to the extract administered during the early phases of an injection regimen, and the clinical response. Dosing is individualized by choice of an initial dose, the schedule of dose build-up, the target maintenance dose, the actual maintenance dose, and the duration of treatment.

The large volume of solution for immunotherapy may produce increased discomfort in the pediatric population. In order to achieve the total dose required, the volume of the dose may need to be divided into more than one injection per visit.²

2.3.1 Dose Build-up

Following the first administration of 0.03 mL of the selected initial dilution of allergenic extract , dosing is increased in 0.03 mL to 0.12 mL increments until 0.3 mL is reached, following which 0.03 mL is administered from the next most concentrated allergen extract or allergen mixture vial in the dilution series. The interval between doses is usually 3 to 7 days during dose build-up. Proceed in this manner until a maintenance dose is reached. The final maintenance dose may not be the target maintenance dose selected at the beginning of therapy.

The following adjustments may be necessary during dose build-up:

- If allergic symptoms or local reactions develop shortly after dose administration, decrease the dose volume to one-half or one-quarter of the maximum dose previously attained.
- If the patient is experiencing any seasonal allergy symptoms, decrease the dose volume to one-half or one‑quarter of the maximum dose previously attained.
- Adjust the dose periodically based on the patient’s tolerance and reaction.
- Decrease the dose if the previous injection resulted in a marked local reaction.
- Repeat the previous dose or reduce the dose at the next administration if local reactions persist for longer than 24 hours.
- Decrease the dose if the previous injection resulted in a systemic reaction.Any evidence of a systemic reaction is an indication for a significant (at least 75%) reduction in the subsequent dose or the cessation of immunotherapy.
- Repeated systemic reactions, however mild, are sufficient reason for the cessation of further attempts to increase the reaction-causing dose.

2.3.2 Maintenance Dose Selection, Adjustments, and Intervals

The maintenance dose is the dose that provides therapeutic efficacy without severe adverse local or systemic reactions. This dose may be limited by adverse reactions and may not be the original targeted maintenance dose. Select a maintenance dose based on the patient's clinical response and tolerance.

- Suggested maintenance dose is 0.3 mL of the undiluted allergen extract. Occasionally, higher doses are necessary to relieve symptoms.
- Maintenance doses larger than 0.3 mL of undiluted allergen extract may cause patient discomfort due to the 50% glycerin content.
- After the maintenance dose is achieved, increase the injection interval to 2 weeks, then 3 weeks, and finally 4 weeks, as tolerated. Administer the maintenance dose at a given interval three or four times before further increasing the interval to assure that no reactions occur. Protection may be lost rapidly if the interval between doses is more than 4 weeks.
  The following adjustments to the maintenance dose may be necessary:
- Withhold immunotherapy and/or reduce dosage, if any of the following conditions exist:
- Severe symptoms of rhinitis and/or asthma. Decrease dose to one-half or one-quarter of the maximum dose previously attained if the patient has any seasonal symptoms.
- Allergic symptoms or a local reaction following the prior dose.
- Infection accompanied by fever.
- Exposure to excessive amounts of clinically relevant allergen prior to a scheduled injection.

In situations prompting dose reduction, a cautious increase in dosage can be attempted once the reduced dose is tolerated.

Decrease the interval between doses if symptoms develop before the next injection is scheduled.

In some patients, the dosage may be increased and/or the dosing interval shortened based on individual responses and dosing requirements. If the onset of symptoms is soon after the initiation of immunotherapy, decrease the interval between each dose.

Changing to a different lot of extract: All extracts can lose allergenic activity over time and extracts vary in allergenic activity. Two different lots of extract could differ substantially in allergenic activity, even if they are the same formula and concentration. The volume of the first dose from the new vial should not exceed 50% of the previous dose. Do not use extracts beyond their expiry date.

Changing to a different formulation of extract or to an extract from a different manufacturer: Decrease the starting dose of the new extract when the extract is the same formula and dilution as the one previously used. In general, a volume dose reduction to 50% of the previous product dose is adequate, but each situation must be evaluated separately considering the patient's history of sensitivity, tolerance of previous injections, and other factors. If the patient tolerates the 50% decrease, then raise the next dose to the previous tolerated dose amount. To re-establish the maintenance dose the starting interval between doses should not be greater than one week.

Prolonged period has elapsed since the last injection: Patients may lose tolerance for allergen injections during prolonged intervals (> 4 weeks) between doses. The duration of tolerance is an individual characteristic and varies from patient to patient. In general, the longer the lapse in the injection schedule, the greater dose reduction required.

Changes made in the extract concentrate formula: Changes other than those listed above such as a difference in extracting fluid (e.g., change from non-glycerin extracts to 50% glycerin extracts), combining two or more stock concentrates, or any other change can affect a patient’s tolerance of the treatment. Extra dilutions are recommended whenever starting a revised formula. The greater the change, the greater the number of dilutions required.

Duration of Treatment

The duration of treatment for immunotherapy has not been established. A period of two to three years of injection therapy constitutes an average minimum course of treatment. Evaluate patients for treatment response at least every 6 to 12 months while they receive immunotherapy.

3 DOSAGE FORMS AND STRENGTHS

Short Ragweed Pollen Allergenic Extract and Short and Giant Ragweed Pollen Mix Allergenic Extracts solution: stock concentrate, labeled in Amb a 1 Units/mL, in a glycerin-preserved extracting fluid, supplied in 5 mL dropper vial, and 10 and 50 mL multidose vials. (3, 16)

Refer to the vial label for the product concentration. (11)

4 CONTRAINDICATIONS

Short Ragweed Pollen and Short and Giant Ragweed Pollen Mix Allergenic Extracts are contraindicated in individuals with the following conditions:

- Severe, unstable or uncontrolled asthma.
- History of any severe systemic reaction to the allergen extract when administered for diagnosis or treatment.
- Medical condition that reduces the ability to survive anaphylaxis.

5 WARNINGS AND PRECAUTIONS

5.1 Anaphylaxis

Anaphylaxis, which may lead to death, can occur in individuals following the administration of Short Ragweed Pollen and Short and Giant Ragweed Pollen Mix allergenic extracts, particularly in the following situations:

- Extreme sensitivity to Short Ragweed Pollen and Short and Giant Ragweed Pollen Mix allergenic extracts.
- Concomitant environmental exposure to allergens.
- Receipt of high doses of the Short Ragweed Pollen and Short and Giant Ragweed Pollen Mix allergenic extracts.
- Receipt of an accelerated build-up schedule (“rush” immunotherapy)
- Change from one lot of a particular Short Ragweed Pollen or Short and Giant Ragweed Pollen Mix allergenic extract to another lot of the same Short Ragweed Pollen or Short and Giant Ragweed Pollen Mix allergenic extract.

Administer Short Ragweed Pollen and Short and Giant Ragweed Pollen Mix allergenic extracts in a healthcare setting under the supervision of a physician prepared to manage anaphylaxis; management may include use of inhaled bronchodilators and use of epinephrine. Short Ragweed Pollen and Short and Giant Ragweed Pollen Mix allergenic extracts may not be suitable for individuals who may be unresponsive to epinephrine or inhaled bronchodilators, such as those taking beta-blockers. See prescribing information for epinephrine for complete information, particularly on medications that blunt or potentiate epinephrine activity. Individuals should remain in the physician’s office for a minimum of 30 minutes after receiving an injection of allergenic extracts, so that any adverse reaction can be observed and properly handled.

5.2 Cross-reactions and Dose Sensitivity

When determining the final dose of an allergen mixture for immunotherapy, consider cross-reactivity among component extracts.

Determine the initial dilution of allergenic extract, starting dose, and progression of dosage based on the patient’s history and results of skin tests [see Dosage and Administration (2)]. Strongly positive skin tests can be indicators for potential adverse reactions.

6 ADVERSE REACTIONS

Common adverse reactions reported for Short Ragweed Pollen Allergenic Extract and Short and Giant Ragweed Pollen Mix Allergenic Extract are:

- Local reactions occurring in 26 to 82% of all patients who receive subcutaneous immunotherapy, at the injection site (e.g., erythema, swelling, pruritus, tenderness and pain).
- Systemic adverse reactions occurring in ≤ 7% of patients who receive subcutaneous immunotherapy (e.g., generalized skin erythema, urticaria, pruritus, angioedema, rhinitis, wheezing, laryngeal edema, hypotension, and shock).Systemic reactions may be fatal.^2

No clinical trials of Short Ragweed Pollen Allergenic Extract and Short and Giant Ragweed Pollen Mix Allergenic Extract have been conducted.

Published studies of allergenic extracts report systemic reactions occurring in fewer than 1% in patients receiving conventional immunotherapy and greater than 36% in patients receiving rush immunotherapy. Most systemic reactions occurred within 30 minutes of injection. However, systemic reactions have been reported to occur up to 2 hours after the final injection with rush schedules. Some reactions have occurred up to 6 hours after skin tests or immunotherapy.^(2, 3)

7 DRUG INTERACTIONS

7.1 Antihistamines

Do not perform skin testing with Short Ragweed Pollen and Short and Giant Ragweed Pollen Mix allergenic extracts within 3 to 10 days of first-generation H1-histamine receptor blockers (e.g., clemastine, diphenhydramine) and second-generation antihistamines (e.g., loratadine, fexofenadine) being used. These products suppress histamine skin test reactions and could mask a positive response.^(1, 2)

7.2 Topical Corticosteroids and Topical Anesthetics

Topical corticosteroids may suppress skin reactivity; therefore, discontinue use at the skin test site for at least 2 to 3 weeks before skin testing. Avoid use of topical local anesthetics at skin test sites because they can suppress flare responses.^(1, 2)

7.3 Tricyclic Antidepressants

Tricyclic antidepressants, such as doxepin, can have potent antihistamine effects and may alter skin test results. Allow 7 to 14 days after discontinuation of tricyclic medication prior to skin testing.^(1, 2)

8 USE IN SPECIFIC POPULATIONS

8.1 Pregnancy

Risk Summary

All pregnancies have a risk of birth defect, loss, or other adverse outcomes. In the U.S. general population, the estimated background risk of major birth defects and miscarriage in clinically recognized pregnancies is 2 to 4% and 15 to 20%, respectively. There are no human or animal data to establish the presence or absence of Short Ragweed Pollen Allergenic Extract and Short and Giant Ragweed Pollen Mix Allergenic Extract-associated risks during pregnancy.

8.2 Lactation

Risk Summary

It is not known whether Short Ragweed Pollen Allergenic Extract and Short and Giant Ragweed Pollen Mix Allergenic Extract are present in human milk. Data are not available to assess the effects of these extracts on the breastfed child or on milk production/excretion. The developmental and health benefits of breastfeeding should be considered along with the mother’s clinical need for allergenic extracts and any potential adverse effects on the breastfed child from the extracts or from the underlying maternal condition.

8.4 Pediatric Use

For use of these products in children younger than 5 years of age, consideration should be given to the patient’s ability to comply and cooperate with receipt of the product and the potential for difficulty in communicating with the child regarding systemic reactions.²

The volume of a dose for immunotherapy may need to be divided for pediatric patients [see Dosage and Administration (2.3)].

8.5 Geriatric Use

Data are not available to determine if subjects 65 years of age and older respond differently to allergen immunotherapy than younger subjects.

11 DESCRIPTION

The expression of concentration applied to Short Ragweed Pollen Allergenic Extract and Short and Giant Ragweed Pollen Mix Allergenic Extract is Amb a 1 Units/mL. Amb a 1 is considered the most important allergen in Short Ragweed and is the basis for standardization. Short Ragweed Pollen Allergenic Extract and Short and Giant Ragweed Pollen Mix Allergenic Extracts are standardized by comparison to reference standards supplied by the Center for Biologics Evaluation and Research (CBER) of the FDA.

Short Ragweed Pollen and Short and Giant Ragweed Pollen Mix allergenic extracts are supplied in a Glycero Cocas extraction solution, which consists of 0.5% sodium chloride for isotonicity, 0.275% sodium bicarbonate as buffer, and 50% glycerin (volume/volume) as preservative.

12 CLINICAL PHARMACOLOGY

12.1 Mechanism of Action

The skin test reaction results from interaction of the introduced allergen and allergen-specific IgE antibodies bound to mast cells, leading to mast cell degranulation and release of histamine, tryptase and other mediators, which results in the formation of the wheal and flare.

The precise mechanisms of action of allergen immunotherapy are not known. Immunologic responses to immunotherapy include changes in allergen-specific IgE levels, allergen-specific IgG levels, and regulatory T cell responses.

14 CLINICAL STUDIES

Studies with aqueous ragweed pollen allergenic extract immunotherapy have demonstrated symptom amelioration in ragweed-allergic individuals.^(4, 5)

15 REFERENCES

1. Bernstein IL, Li JT, Bernstein Dl, et al. Allergy diagnostic testing: an updated practice parameter. Ann Allergy Asthma Immunol. 2008 Mar;100: S1-148.

2. Cox L, Nelson H, Lockey R, Calabria C, Chacko T, Finegold I, et al. Allergen immunotherapy: A practice parameter third update. J Allergy Clin Immunol. 2011 Jan;127: S1-55.

3. Greineder DK. Risk management in allergen immunotherapy. J Allergy Clin Immunol. 1996 Dec;98(6 Pt 3):S330‑4.

4. Norman PS, Winkenwerder WL, Lichtenstein LM. Immunotherapy of hay fever with ragweed antigen E: comparisons with whole pollen extract and placebos. J Allergy. 1968; 42(2):93-108.

5. Reisman RE, Wicher K, Arbesman CE. Immunotherapy with antigen E. J Allergy. 1969 Aug;44(2):82-95.

16 HOW SUPPLIED/STORAGE AND HANDLING

16.1 How Supplied

Short Ragweed Pollen Allergenic Extract and Short and Giant Ragweed Pollen Mix Allergenic Extract are supplied as 50% glycerin stock concentrates labeled in Amb a 1 units/mL and provided in 10 milliliter and 50 milliliter vials for use in percutaneous skin testing, intradermal skin testing, and subcutaneous immunotherapy. These extracts may also be supplied in 5 milliliter dropper vials for percutaneous testing only.

These products are supplied as listed in Table 2.

Table 2: Available Products

SHORT RAGWEED POLLEN ALLERGENIC EXTRACT
NDC | Strength/Container
65044-2297-1 | 200 Amb a 1 Units/mL, 5 mL dropper vial for percutaneous testing
65044-2297-2 | 200 Amb a 1 Units/mL, 10 mL multi-dose vial
65044-2297-4 | 200 Amb a 1 Units/mL, 50 mL multi-dose vial
SHORT AND GIANT RAGWEED POLLEN ALLERGENIC EXTRACT
NDC | Strength/Container
65044-2315-1 | 100 Amb a 1 Units/mL, 5 mL dropper vial for percutaneous testing
65044-2315-2 | 100 Amb a 1 Units/mL, 10 mL multi-dose vial
65044-2315-4 | 100 Amb a 1 Units/mL, 50 mL multi-dose vial

16.2 Storage and Handling

Store extracts at 2°C to 8°C (36°F to 46°F).

17 PATIENT COUNSELING INFORMATION

Instruct patients to remain in the office under observation for a minimum of 30 minutes after an injection or longer, if deemed necessary for the individual.

Inform patients that reactions may occur more than 30 minutes after skin testing or an injection.

Instruct patient to recognize the following symptoms as systemic adverse reactions and seek emergency medical care right away if any of these symptoms occur:

- Unusual swelling and/or tenderness at the injection site
- Hives or itching of the skin
- Swelling of face and/or mouth
- Sneezing, coughing, or wheezing
- Shortness of breath
- Nausea
- Dizziness or faintness

Manufacturer:

Jubilant HollisterStier LLC

Spokane, WA 99207 U.S.A.

U.S. License No. 1272

PRINCIPAL DISPLAY PANEL

Short Ragweed 5mL Carton 200 Amb a 1 units-mL
Short Ragweed 5mL Container 200 Amb a 1 units-mL

PRINCIPAL DISPLAY PANEL

Short Ragweed 10mL Carton 200 Amb a 1 units-mL
Short Ragweed 10mL Container 200 Amb a 1 units-mL

PRINCIPAL DISPLAY PANEL

Short Ragweed 50mL Carton 200 Amb a 1 units-mL
Short Ragweed 50mL Container 200 Amb a 1 units-mL

PRINCIPAL DISPLAY PANEL

Ragweed Mix GS 5mL Carton 100 Amb a 1 units-mL
Ragweed Mix GS 5mL Container 100 Amb a 1 units-mL

PRINCIPAL DISPLAY PANEL

Ragweed Mix GS 10mL Carton 100 Amb a 1 units-mL
Ragweed Mix GS 10mL Container 100 Amb a 1 units-mL

PRINCIPAL DISPLAY PANEL

Ragweed Mix GS 50mL Carton 100 Amb a 1 units-mL
Short Ragweed 50mL Container 200 Amb a 1 units-mL